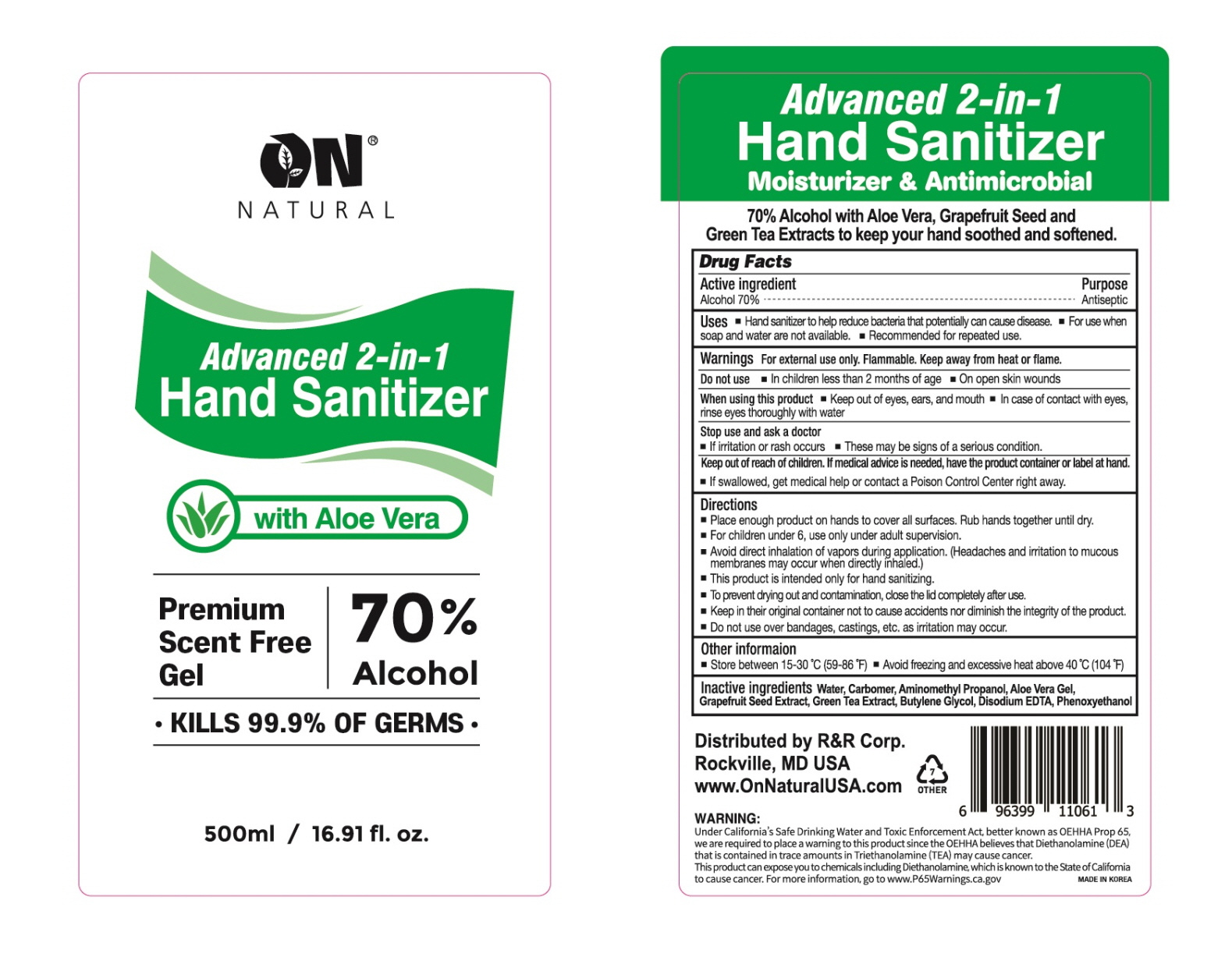 DRUG LABEL: Advanced 2 in 1 Hand Sanitizer
NDC: 74923-100 | Form: GEL
Manufacturer: THE SUN CO.LTD
Category: otc | Type: HUMAN OTC DRUG LABEL
Date: 20200604

ACTIVE INGREDIENTS: Alcohol 350 mL/500 mL
INACTIVE INGREDIENTS: Water; CARBOMER HOMOPOLYMER, UNSPECIFIED TYPE; AminomethylPropanol; ALOE VERA LEAF; CITRUS PARADISI SEED; GREEN TEA LEAF; Butylene Glycol; EDETATE DISODIUM ANHYDROUS; Phenoxyethanol

ACTIVE INGREDIENT

Alcohol 70.0%

INACTIVE INGREDIENTS

Water, Carbomer, Aminomethyl Propanol, Aloe Vera Gel, Grapefruit Seed Extract. Green Tea Extract, Butylene Glycol, Disodium EDTA, Phenoxyethanol

PURPOSE

Antiseptic

WARNINGS

For external use only. Flammable. Keep away from heat and flame.

Do not use ■ In children less than 2 months of age. ■ On open skin wounds

When using this product ■ Keep out of eyes, ears, and mouth ■ In case of contact with eyes, rinse eyes thoroughly with water.

Stop use and ask a doctor
■ If irritation or rash occurs ■ These may be signs of a serious condition.

KEEP OUT OF REACH OF CHILDREN

If medical advice is needed, have the product container or label at hand.
■ If swallowed, get medical help or contact a Poison Control Center right away.

Uses

■ Hand sanitizer to help reduce bacteria that potentially can cause disease.
■ For use when soap and water are not available.
■ Recommended for repeated use.

Directions

■ Place enough product on hands to cover all surfaces. Rub hands together until dry.
■ For children under 6, use only under adult supervision
■ Avoid direct inhalation of vapors during application (Headaches and irritation to mucous membranes may occur when directly inhaled.)
■ This product is intended only for hand sanitizing.
■ To prevent drying out and contamination, close the lid completely after use.
■ Keep in their original container not to cause accidents nor diminish the integrity of the product.
■ Do not use over bandages, castings, etc. ad irritation may occur.

Other Information

■ Store below 43°C (110°F)
■ May discolor certain fabrics or surfaces

QUESTIONS

www.onnaturalusa.com